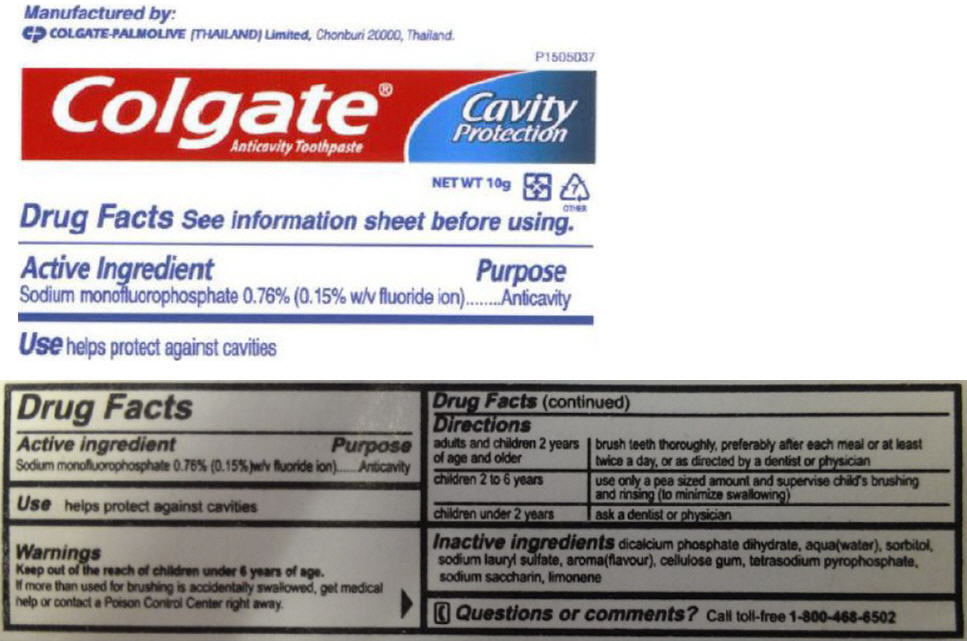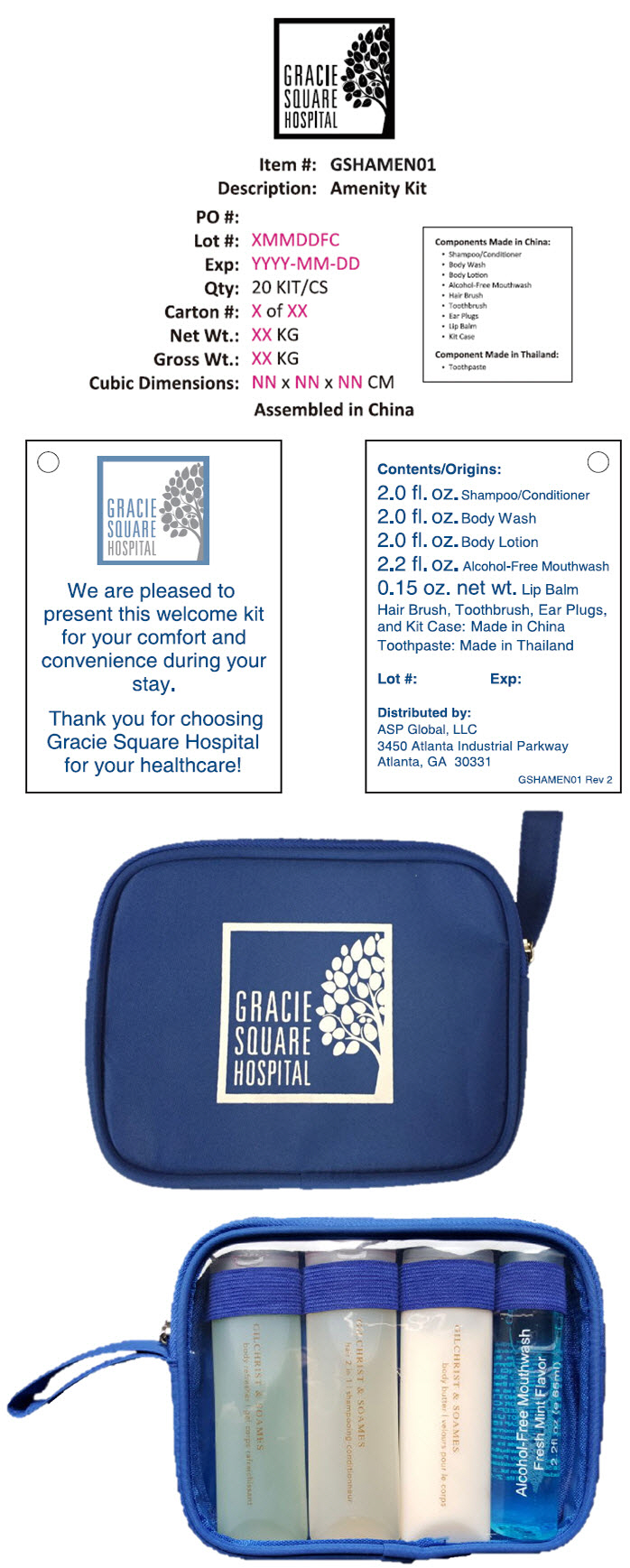 DRUG LABEL: Gracie Square Hospital Amenity
NDC: 59448-101 | Form: KIT | Route: DENTAL
Manufacturer: ASP Global, LLc
Category: otc | Type: HUMAN OTC DRUG LABEL
Date: 20251229

ACTIVE INGREDIENTS: Sodium Monofluorophosphate 7.6 mg/1 g
INACTIVE INGREDIENTS: Dibasic Calcium Phosphate Dihydrate; Water; Sorbitol; Sodium Lauryl Sulfate; Sodium Pyrophosphate; Saccharin Sodium

Gracie Square Hospital Amenity Kit

Colgate® Anticavity Toothpaste

Drug Facts

Active ingredient

Sodium monofluorophosphate 0.76% (0.15%)w/v fluoride ion)

Purpose

Anticavity

Use

helps protect against cavities

Warnings

KEEP OUT OF REACH OF CHILDREN

Keep out of the reach of children under 6 years of age.

If more than used for brushing is accidentally swallowed, get medical help or contact a Poison Control Center right away.

Directions

adults and children 2 years of age and older | brush teeth thoroughly, preferably after each meal or at least twice a day, or as directed by a dentist or physician
children 2 to 6 years | use only a pea sized amount and supervise child's brushing and rinsing (to minimize swallowing)
children under 2 years | ask a dentist or physician

Inactive ingredients

dicalcium phosphate dihydrate, aqua(water), sorbitol, sodium lauryl sulfate, aroma(flavour), cellulose gum, tetrasodium pyrophosphate, sodium saccharin, limonene

Questions or comments?

Call toll-free 1-800-468-6502

Manufactured by:
COLGATE-PALMOLIVE (THAILAND) Limited, Chonburi 20000, Thailand.

PRINCIPAL DISPLAY PANEL - 10 g Tube Label

Colgate®
Anticavity Toothpaste

Cavity
Protection

NET WT 10g

PRINCIPAL DISPLAY PANEL - Kit Label

GRACIE
SQUARE
HOSPITAL

Item #: GSHAMEN01

Description: Amenity Kit

PO #:

Lot #: XMMDDFC

Exp: YYYY-MM-DD

Qty: 20 KIT/CS

Carton #: X of XX

Net Wt.: XX KG

Gross Wt.: XX KG

Cubic Dimensions: NN x NN x NN CM

Assembled in China

Components Made in China:

- Shampoo/Conditioner
- Body Wash
- Body Lotion
- Alcohol-Free Mouthwash
- Hair Brush
- Toothbrush
- Ear Plugs
- Lip Balm
- Kit Case

Component Made in Thailand:

- Toothpaste

GRACIE
SQUARE
HOSPITAL

We are pleased to
present this welcome kit
for your comfort and
convenience during your
stay.

Thank you for choosing
Gracie Square Hospital
for your healthcare!

Contents/Origins:

2.0 fl. oz. Shampoo/Conditioner
2.0 fl. oz. Body Wash
2.0 fl. oz. Body Lotion
2.2 fl. oz. Alcohol-Free Mouthwash
0.15 oz. net wt. Lip Balm
Hair Brush, Toothbrush, Ear Plugs,
and Kit Case: Made in China
Toothpaste: Made in Thailand

Lot #:
Exp:

Distributed by:
ASP Global, LLC
3450 Atlanta Industrial Parkway
Atlanta, GA 30331

GSHAMEN01 Rev 2

GRACIE
SQUARE
HOSPITAL